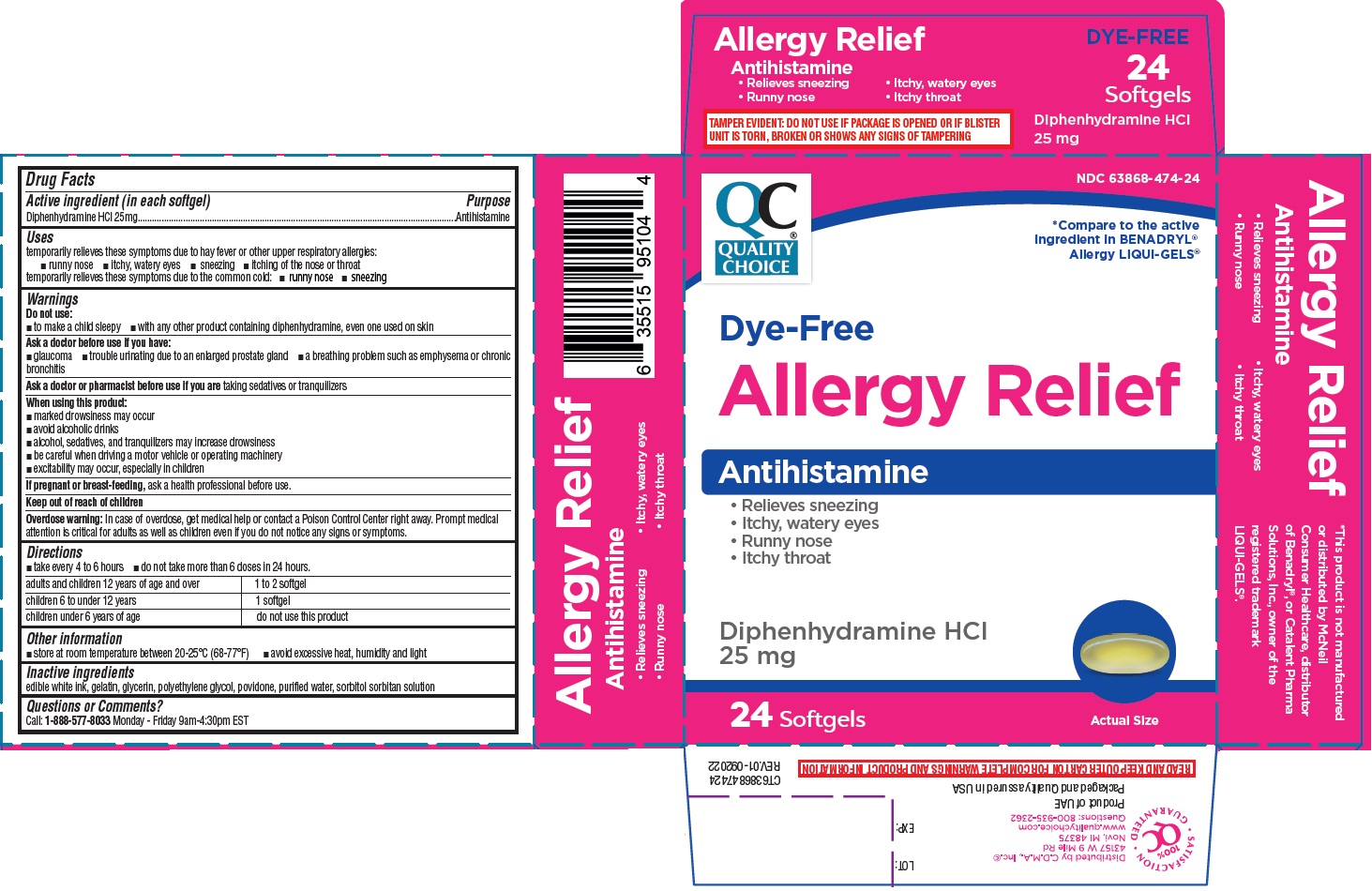 DRUG LABEL: Allergy Relief Antihistamine
NDC: 63868-474 | Form: CAPSULE, LIQUID FILLED
Manufacturer: CDMA Inc
Category: otc | Type: HUMAN OTC DRUG LABEL
Date: 20241216

ACTIVE INGREDIENTS: DIPHENHYDRAMINE HYDROCHLORIDE 25 mg/1 1
INACTIVE INGREDIENTS: GELATIN, UNSPECIFIED; GLYCERIN; POLYETHYLENE GLYCOL, UNSPECIFIED; POVIDONE, UNSPECIFIED; WATER; SORBITOL; SORBITAN

Allergy Relief Antihistamine

Drug Facts

Active ingredient (in each softgel)

Diphenhydramine HCl 25mg

Purpose

Antihistamine

Uses

temporarily relieves these symptoms due to hay fever or other upper respiratory allergies:
• runny nose • itchy, watery eyes • sneezing • itching of the nose or throat
temporarily relieves these symptoms due to the common cold: • runny nose • sneezing

Warnings

Do not use:
• to make a child sleepy • with any other product containing diphenhydramine, even one used on skin

Ask a doctor before use if you have:
• glaucoma • trouble urinating due to an enlarged prostate gland • a breathing problem such as emphysema or chronic bronchitis

Ask a doctor or pharmacist before use if you are taking sedatives or tranquilizers

When using this product:
• marked drowsiness may occur
• avoid alcoholic drinks
• alcohol, sedatives, and tranquilizers may increase drowsiness
• be careful when driving a motor vehicle or operating machinery
• excitability may occur, especially in children

If pregnant or breast-feeding, ask a health professional before use.

Keep out of reach of children

OVERDOSAGE

Overdose warning: In case of overdose, get medical help or contact a Poison Control Center right away. Prompt medical attention is critical for adults as well as children even if you do not notice any signs or symptoms.

Directions

• take every 4 to 6 hours • do not take more than 6 doses in 24 hours.

adults and children 12 years of age and over | 1 to 2 softgel
children 6 to under 12 years | 1 softgel
children under 6 years of age | do not use this product

Other information

• store at room temperature between 20-25°C (68-77°F) • avoid excessive heat, humidity and light

Inactive ingredients

edible white ink, gelatin, glycerin, polyethylene glycol, povidone, purified water, sorbitol sorbitan solution

Questions or Comments?

Call: 1-888-577-8033 Monday - Friday 9am-4:30pm EST

QC®
QUALITY CHOICE

*Compare to the active Ingredient in BENADRYL® Allergy LIQUI-GELS®

Dye-Free

• Relieves sneezing
• Itchy, watery eyes
• Runny nose
• Itchy throat

TAMPER EVIDENT: DO NOT USE IF PACKAGE IS OPENED OR IF BLISTER UNIT IS TORN, BROKEN OR SHOWS ANY SIGNS OF TAMPERING

*This product is not manufactured or distributed by McNeil Consumer Healthcare, distributor of Benadryl®,or Catalent Pharma Solutions, Inc., owner of the registered trademark LIQUI-GELS®.

QC 100% SATISFACTION GUARANTEED

Distributed by C.D.M.A., Inc.©
43157 W 9 Mile Rd
Novi, MI 48375
www.qualitychoice.com
Questions: 800-935-2362

Product of UAE

Packaged and Quality assured in USA

READ AND KEEP OUTER CARTON FOR COMPLETE WARNINGS AND PRODUCT INFORMATION

REV.01-092022